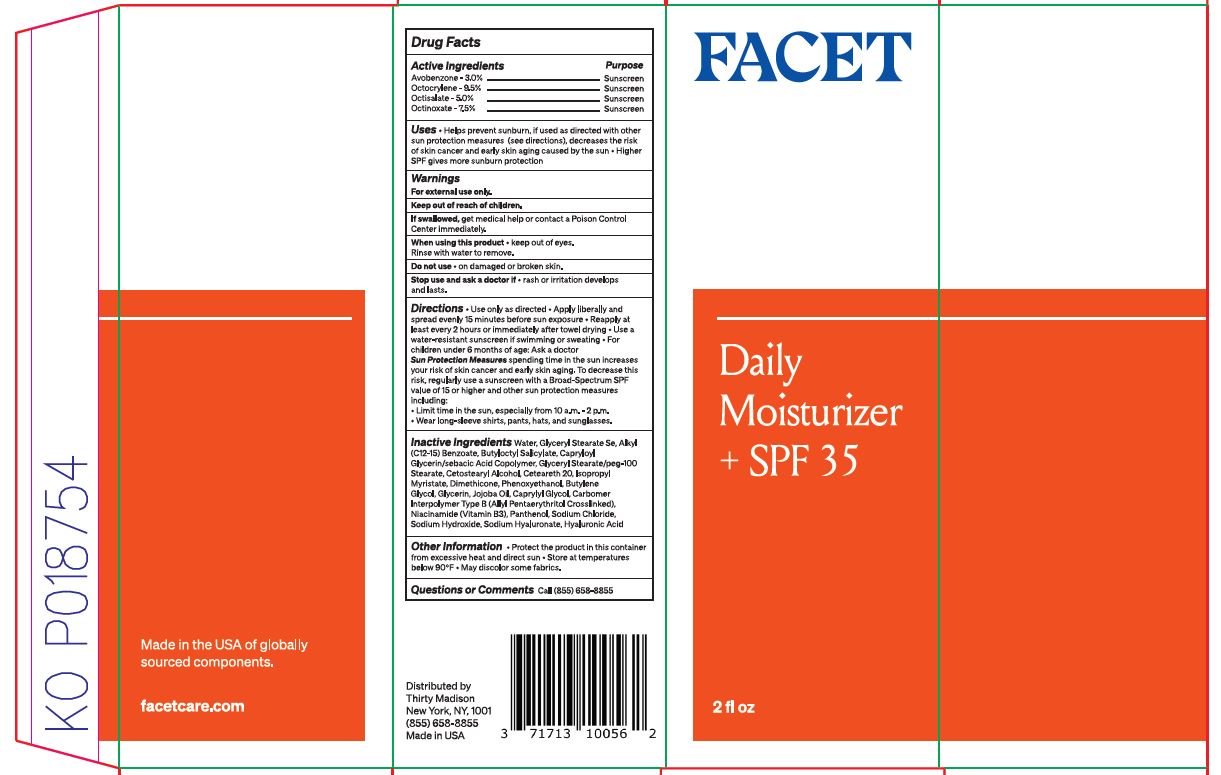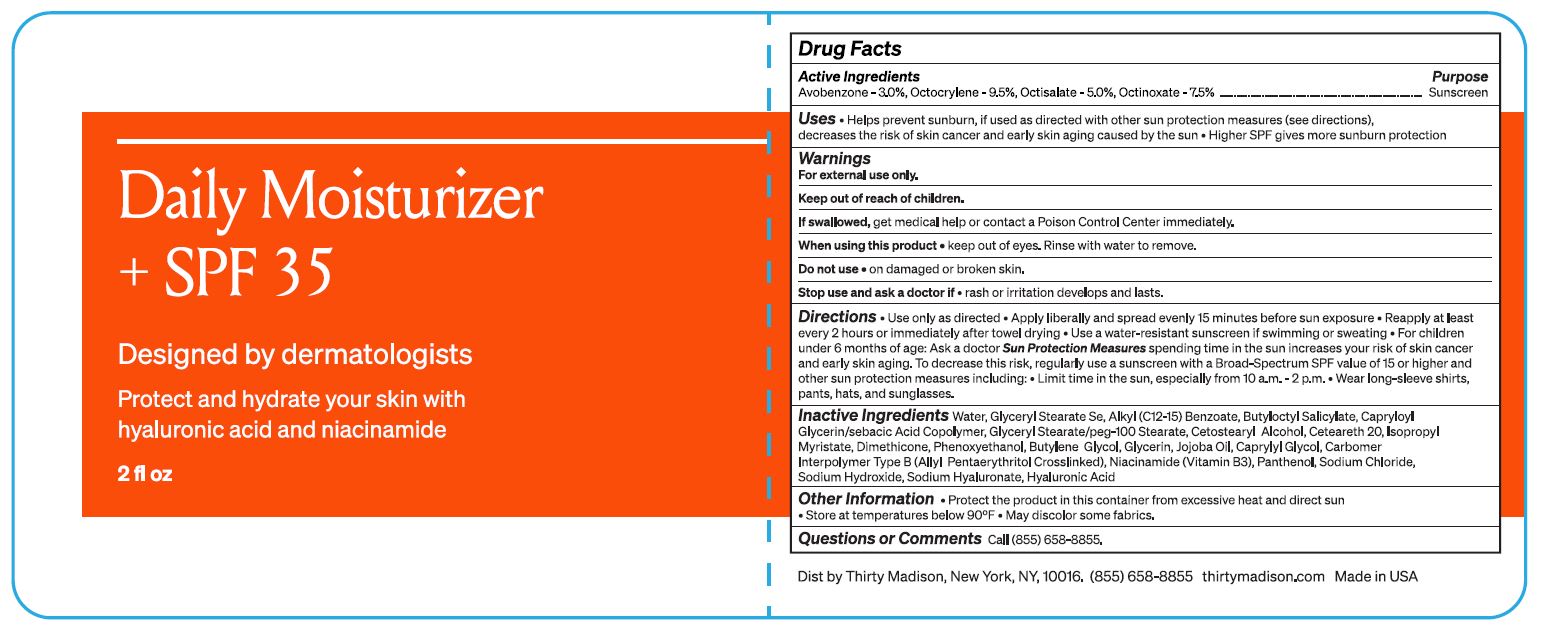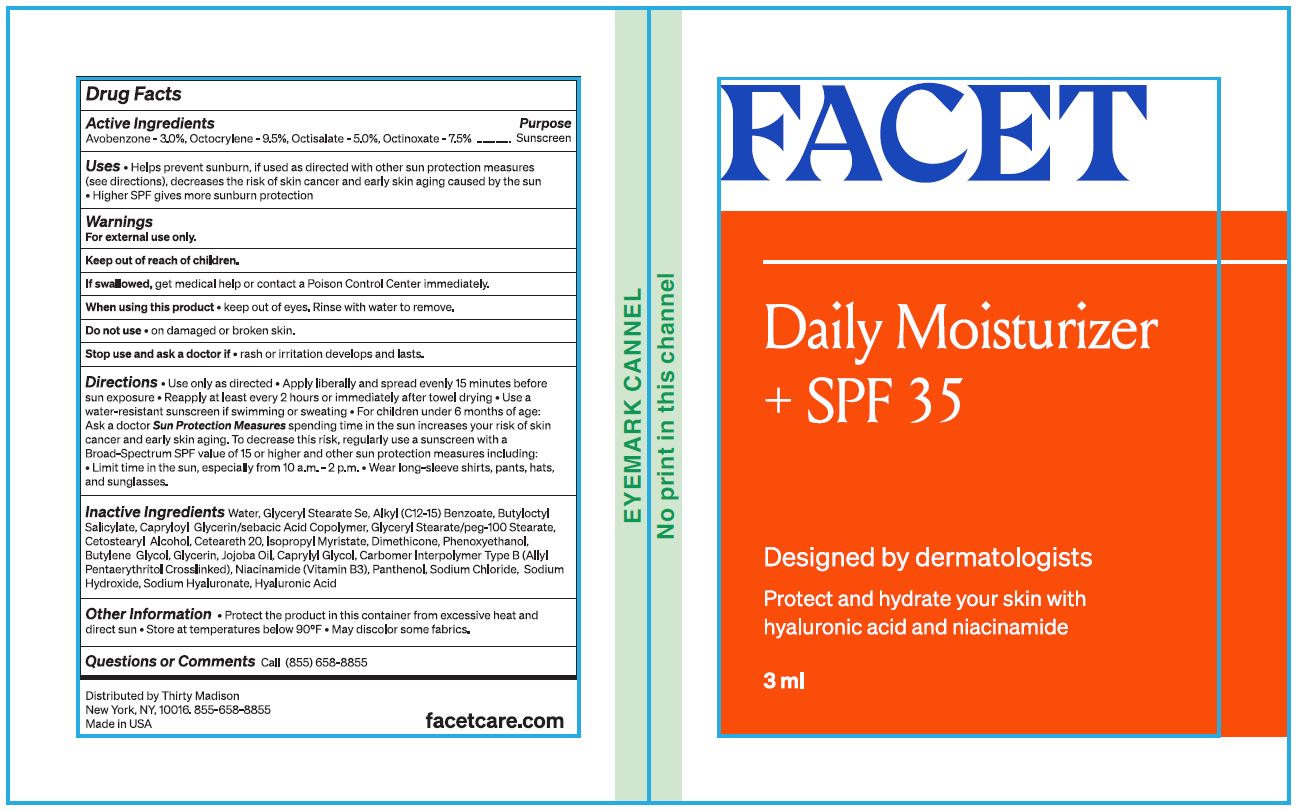 DRUG LABEL: Facet Daily Moisturizer SPF 35
NDC: 52261-0800 | Form: LOTION
Manufacturer: Cosco International, Inc.
Category: otc | Type: HUMAN OTC DRUG LABEL
Date: 20220901

ACTIVE INGREDIENTS: AVOBENZONE 0.03 kg/1 kg; OCTISALATE 0.05 kg/1 kg; OCTOCRYLENE 0.095 kg/1 kg; OCTINOXATE 0.075 kg/1 kg
INACTIVE INGREDIENTS: ALKYL (C12-15) BENZOATE; BUTYLENE GLYCOL; BUTYLOCTYL SALICYLATE; CAPRYLOYL GLYCERIN/SEBACIC ACID COPOLYMER (2000 MPA.S); DIMETHICONE 350; SODIUM HYDROXIDE; NIACINAMIDE; GLYCERIN; SODIUM CHLORIDE; GLYCERYL STEARATE SE; WATER; ISOPROPYL MYRISTATE; CAPRYLYL GLYCOL; PHENOXYETHANOL; GLYCERYL STEARATE/PEG-100 STEARATE; PANTHENOL; HYALURONATE SODIUM; HYALURONIC ACID; CARBOMER COPOLYMER TYPE B (ALLYL PENTAERYTHRITOL CROSSLINKED); CETOSTEARYL ALCOHOL; POLYOXYL 20 CETOSTEARYL ETHER; JOJOBA OIL

Facet Daily Moisturizer + SPF 35

Drug Facts

Active Ingredient....................Purpose

Avobenxone 3.00%..................Sunscreen

Octocrylene 9.50%..................Sunscreen

Octilsalate 5.00%....................Sunscreen

Octinoxate 7.50%....................Sunscreen

Uses

- Helps prevent sunburn. If used as directed with other sun protection measures, (see directions), decreases the risk of skin cancer and early skin aging caused by the sun.
- Higher SPF gives more subburn protection

Warnings

For external use only.

Keep out of reach of children.

If swallowed, get medical help or contact a Poison Control Center immediately.

When using this product

- keep out of eyes. Rinse with water to remove.

Do not use

- on damaged or broken skin.

Stop use and ask a doctor if

- rash or irritation develops and lasts.

Directions

- Use only as directed
- Apply liberally and spread evenly 15 minutes before sun exposure
- Reapply at least every 2 hours or immediately after towel drying
- Use a water-resistant sunscreen if swimming or sweating
- For children under 6 months of age: Ask a doctor

Sun Protection Measures spending time in the sun increases your risk of skin cancer and early skin aging. To decrease this risk, regularly use a sunscreen with a Broad-Spectrum SPF value of 15 or higher and other sun protection measures including:

- limit time in the sun, especially from 10 a.m. - 2 p.m.
- Wear long-sleeved shirts, pants, hats and sunglasses.

Inactive Ingredients

Water, Glyceryl Stearate SE, Alkyl (C12-15) Benzoate, Butyloctyl Salicylate, Capryloyl Glycerin/Sebacic Acid Copolymer, Glyceryl Stearate/PEG-100 Stearate, Cetostearyl Alcohol, Ceteareth 20, Isopropyl Myristate, Dimethicone, Phenoxyethanol, Butylene Glycol, Glycerin, Jojoba Oil, Caprylyl Glycol, Carbomer Interpolymer Type B (Allyl Pentaerythritol Crosslinked), Niacinamide (vitamin B3), Panthenol, Sodium Chloride, Sodium Hydroxide, Sodium Hyaluronate, Hyaluronic Acid

Other Information

- Protect the product in this container from excessuve heat and direct sun
- Store at temperatures below 90°F
- May discolor some fabrics.

Questions or Comments?

Call (855) 658-8855

Distributed by

Thirty Madison

New York, NY, 1001

(855) 658-8855

Made in USA